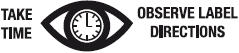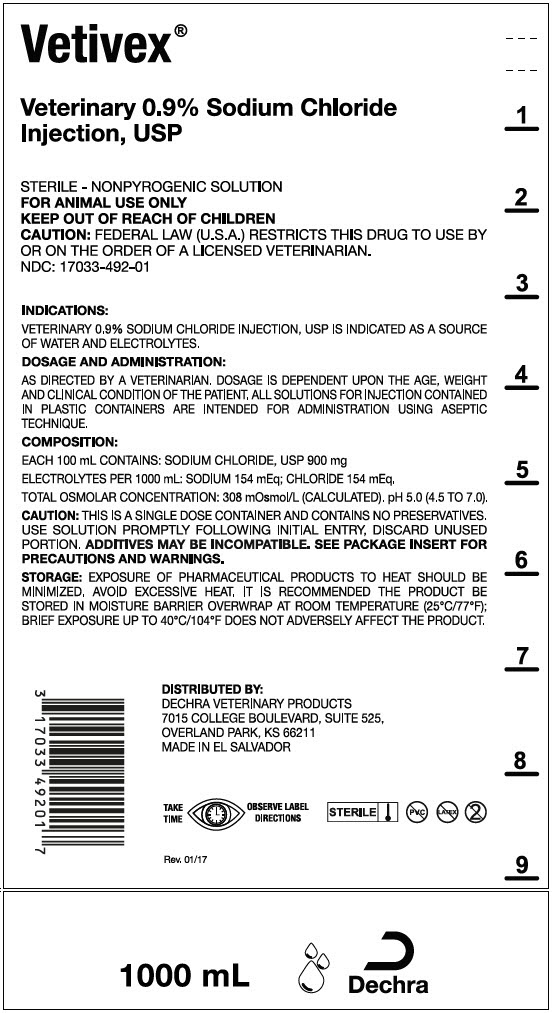 DRUG LABEL: VETIVEX 
NDC: 17033-492 | Form: INJECTION, SOLUTION
Manufacturer: Dechra Veterinary Products
Category: animal | Type: PRESCRIPTION ANIMAL DRUG LABEL
Date: 20200909

ACTIVE INGREDIENTS: sodium chloride 9 mg/1 mL
INACTIVE INGREDIENTS: Water

Vetivex®
Veterinary 0.9% Sodium Chloride Injection, USP

For Animal Use Only

Description:

Veterinary 0.9% Sodium Chloride Injection, USP is a sterile, nonpyrogenic solution for fluid and electrolyte replenishment in single dose containers for parenteral administration. It contains no antimicrobial agents. Discard unused portion.

Table 1 Veterinary 0.9% Sodium Chloride Injection, USP
Size (mL) | Composition (mg/100mL) |  |  | Ionic Concentration (mEq/L)
Size (mL) | Sodium Chloride, USP (NaCl) | Osmolarity (mOsmol/L) (Calculated) | pH | Sodium | Chloride
250 | 900 | 308 | 5.0 (4.5 to 7.0) | 154 | 154
500 | 900 | 308 | 5.0 (4.5 to 7.0) | 154 | 154
1000 | 900 | 308 | 5.0 (4.5 to 7.0) | 154 | 154
3000 | 900 | 308 |  | 154 | 154

Clinical Pharmacology:

Veterinary 0.9% Sodium Chloride Injection, USP has value as a source of water and electrolytes. It is capable of inducing diuresis depending on the clinical condition of the patient.

Indications and Usage:

Veterinary 0.9% Sodium Chloride Injection, USP is indicated as a source of water and electrolytes.

Warnings:

Veterinary 0.9% Sodium Chloride Injection, USP should be used with great care, if at all, in patients with congestive heart failure, severe renal insufficiency, and in clinical states in which there exists edema with sodium retention.

The parenteral administration of Veterinary 0.9% Sodium Chloride Injection, USP can cause fluid and/or solute overloading resulting in dilution of serum electrolyte concentrations, overhydration, congested states, or pulmonary edema. The risk of dilutional states is inversely proportional to the electrolyte concentrations of the injections. The risk of solute overload causing congested states with peripheral and pulmonary edema is directly proportional to the electrolyte concentrations of the injection.

In patients with diminished renal function, administration of Veterinary 0.9% Sodium Chloride Injection, USP may result in sodium retention.

Adverse Reactions:

Reactions which may occur because of the solution or the technique of administration include febrile response, infection at the site of injection, venous thrombosis or phlebitis extending from the site of injection, extravasation, and hypervolemia. If an adverse reaction does occur, discontinue the infusion, evaluate the patient, institute appropriate therapeutic countermeasures, and save the remainder of the fluid for examination if deemed necessary.

Precautions:

Clinical evaluation and periodic laboratory determinations are necessary to monitor changes in fluid balance, electrolyte concentrations, and acid base balance during prolonged parenteral therapy or whenever the condition of the patient warrants such evaluation.

Caution must be exercised in the administration of Veterinary 0.9% Sodium Chloride Injection, USP to patients receiving corticosteroids or corticotropin. Do not administer unless solution is clear and seal is intact.

Dosage and Administration:

As directed by a veterinarian. Dosage is dependent upon the age, weight and clinical condition of the patient, as well as laboratory determinations.

Parenteral drug products should be inspected visually for particulate matter and discoloration prior to administration whenever solution and container permit.

All solutions for injection contained in plastic containers are intended for administration using sterile equipment and aseptic technique. Additives may be incompatible. Complete information is not available. Those additives known to be incompatible should not be used. Consult with pharmacist, if available. If, in the informed judgement of the veterinarian, it is deemed advisable to introduce additives, use aseptic technique. Mix thoroughly when additives have been introduced.

Do not store solutions containing additives. Discard unused portion.

Overdosage:

In an event of overhydration or solute overload, re-evaluate the patient and institute appropriate corrective measures.

See Warnings, Adverse Reactions and Precautions.

How Supplied

Veterinary 0.9% Sodium Chloride Injection, USP is supplied in plastic bags as follows:

NDC Code | Volume
17033-492-25 | 250 mL
17033-492-50 | 500 mL

NDC Code | Volume
17033-492-01 | 1000 mL [PVC Free, DEHP Free and Latex Free Bag.]
17033-492-03 | 3000 mL [The plastic container is fabricated from a specially formulated polyvinyl chloride. The amount of water that can permeate from inside the container into the overwrap is insufficient to affect the solution significantly. Solutions in contact with the plastic container can leach out certain of its chemical components in very small amounts within the expiration period, e.g., di-2-ethylhexyl phthalate (DEHP), up to 5 parts per million. However, the safety of the plastic has been confirmed in animals according to USP biological tests for plastic containers, as well as tissue culture toxicity studies.]

STORAGE AND HANDLING

STORAGE: Exposure of pharmaceutical products to heat should be minimized. Avoid excessive heat.

It is recommended the product be stored in the moisture barrier overwrap at room temperature (25°C/77°F); brief exposure up to 40°C/104°F does not adversely affect the product.

Directions for use of plastic container

To Open

Tear overwrap down side at slit and remove solution bag. Some opacity of the plastic due to moisture absorption during the sterilization process may be observed. This is normal and does not affect the solution quality or safety. The opacity will diminish gradually, Check for minute leaks by squeezing inner bag firmly. If leaks are found, discard solution as sterility may be impaired.

If supplemental medication is desired, follow directions below.

Preparation for Administration

1. Suspend container from eyelet support.
2. Remove protector from outlet port at bottom of container.
3. Attach administration set. Refer to complete directions accompanying set.

To add Medication

WARNING: Additives may be incompatible.

To add medication before solution administration

1. Prepare medication site.
2. Using syringe with 19 to 22 gauge needle, puncture resealable medication port and inject.
3. Mix solution and medication thoroughly. For high density medication such as potassium chloride, squeeze ports while ports are upright and mix thoroughly.

To add medication during solution administration

1. Close clamp on the administration set to stop the flow to the patient.
2. Prepare medication site.
3. Using syringe with 19 to 22 gauge needle, puncture resealable medication port and inject.
4. Remove container from IV pole and/or turn to an upright position.
5. Evacuate both ports by squeezing them while container is in the upright position.
6. Mix solution and medication thoroughly.
7. Return container to in-use position and continue administration.

CAUTION: Federal law (U.S.A.) restricts this drug to use by or on the order of a licensed veterinarian.

DISTRIBUTED BY:
Dechra Veterinary Products
7015 College Boulevard, Suite 525 Overland Park, KS 66211
Made in El Salvador.
For a copy of the Safety Data Sheet (SDS) or to report adverse reactions call
Dechra Veterinary Products at (866) 933-2472.
© 2017 Dechra Ltd.
VETIVEX® is a trademark of Dechra Ltd; all rights reserved.

Rev. 10/17

PRINCIPAL DISPLAY PANEL - 1000 mL Container Label

Vetivex®
Veterinary 0.9% Sodium Chloride
Injection, USP

STERILE - NONPYROGENIC SOLUTION

FOR ANIMAL USE ONLY

KEEP OUT OF REACH OF CHILDREN

CAUTION: FEDERAL LAW (U.S.A.) RESTRICTS THIS DRUG TO USE BY
OR ON THE ORDER OF A LICENSED VETERINARIAN.

NDC: 17033-492-01

1000 mL
Dechra